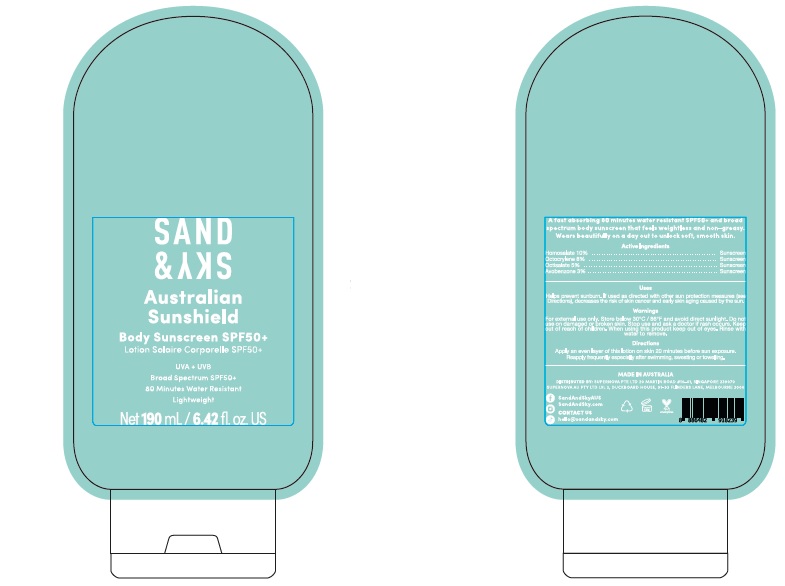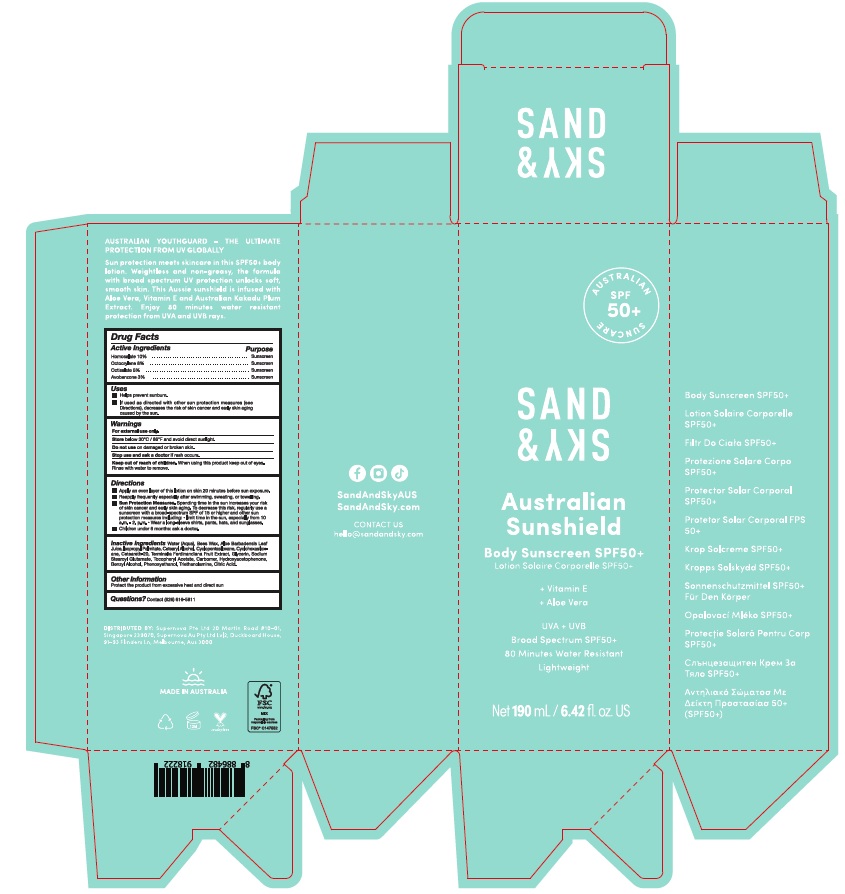 DRUG LABEL: Sand Sky Australian Sunshield Body Sunscreen SPF50 plus
NDC: 82931-004 | Form: LOTION
Manufacturer: Supernova USA Inc.
Category: otc | Type: HUMAN OTC DRUG LABEL
Date: 20221101

ACTIVE INGREDIENTS: HOMOSALATE 10 g/100 mL; OCTOCRYLENE 8 g/100 mL; OCTISALATE 5 g/100 mL; AVOBENZONE 3 g/100 mL
INACTIVE INGREDIENTS: WATER; YELLOW WAX; ALOE VERA LEAF; ISOPROPYL PALMITATE; CETOSTEARYL ALCOHOL; CYCLOMETHICONE 5; CYCLOMETHICONE 6; POLYOXYL 20 CETOSTEARYL ETHER; HYDROXYACETOPHENONE; CARBOMER HOMOPOLYMER, UNSPECIFIED TYPE; BENZYL ALCOHOL; PHENOXYETHANOL; SODIUM STEAROYL GLUTAMATE; TROLAMINE; .ALPHA.-TOCOPHEROL ACETATE; GLYCERIN; KAKADU PLUM; CITRIC ACID MONOHYDRATE

SAND & SKY AUSTRALIAN SUNSHIELD BODY SUNSCREEN SPF50+

Drug Facts

ACTIVE INGREDIENT

PURPOSE

Active Ingredients
Homosalate 10%
Octocrylene 8%
Octisalate 5%
Avobenzone 3%

Purpose
Sunscreen
Sunscreen
Sunscreen
Sunscreen

Uses

- Helps prevent sunburn.
- If used as directed with other sun protection measures (see Directions), decreases the risk of skin cancer and early skin aging caused by the sun.

Warnings

For external use only.

Store below 30°C / 86°F and avoid direct sunlight.

Do not use on damaged or broken skin.

Stop use and ask a doctor if rash occurs.

Keep out of reach of children. When using this product keep out of eyes. Rinse with water to remove.

Directions

- Apply an even layer of this lotion on skin 20 minutes before sun exposure.
- Reapply frequently especially after swimming, swaeting, or towelling.
- Sun Protection Measures. Spending time in the sun increases your risk of skin cancer and early skin aging. To decrease this risk, regularly use a sunscreen with a broad-spectrum SPF of 15 or higher and other sun protection measures including:
  - Limit time in the sun, especially from 10 a.m. - 2. p.m.
  - Wear a long-sleeve shirts, pants, hats, and sunglasses.
- Children under 6 months: ask a doctor.

INACTIVE INGREDIENT

Inactive ingredients Water (Aqua), Bees Wax, Aloe Barbadensis Leaf Juice, Isopropyl Palmitate, Cetearyl Alcohol, Cyclopentasiloxane, Cyclohexasiloxane, Ceteareth-20, Terminalia Ferdinandiana Fruit Extract, Glycerin, Sodium Stearoyl Glutamate, Tocopheryl Acetate, Carbomer, Hydroxyacetophenone, Benzyl Alcohol, Phenoxyethanol, Triethanolamine, Citric Acid.

Other information

Protect the product from excessive heat and direct sun

Questions? Contact (626) 616-5811

PRINCIPAL DISPLAY PANEL

SAND
& SKY

Australian
Sunshield

Body Sunscreen SPF50+
Lotion Solaire Corporelle SPF50+

UVA + UVB
Board Spectrum SPF50+
80 Minutes Water Resistant
Lightweight

Net 190 mL / 6.42 fl. oz. US

PRINCIPAL DISPLAY PANEL

SAND
& SKY

Australian
Sunshield

Body Sunscreen SPF50+
Lotion Solaire Corporelle SPF50+

+ Vitamin E
+ Aloe Vera

UVA + UVB
Board Spectrum SPF50+
80 Minutes Water Resistant
Lightweight

Net 190 mL / 6.42 fl. oz. US